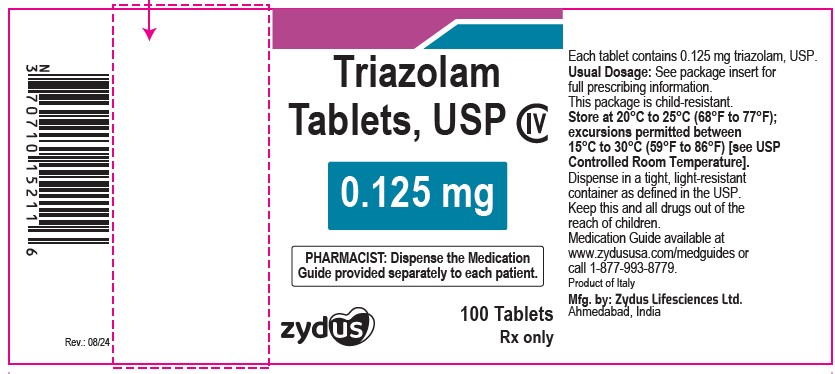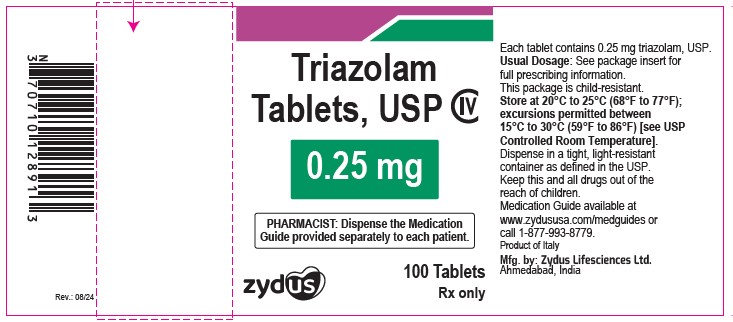 DRUG LABEL: Triazolam
NDC: 70771-1162 | Form: TABLET
Manufacturer: Zydus Lifesciences Limited
Category: prescription | Type: HUMAN PRESCRIPTION DRUG LABEL
Date: 20240814
DEA Schedule: CIV

ACTIVE INGREDIENTS: TRIAZOLAM 0.25 mg/1 1
INACTIVE INGREDIENTS: D&C RED NO. 27; FD&C BLUE NO. 1; LACTOSE MONOHYDRATE; MAGNESIUM STEARATE; MICROCRYSTALLINE CELLULOSE; POVIDONE; SILICON DIOXIDE; SODIUM LAURYL SULFATE; STARCH, CORN

Triazolam Tablets, USP CIV

PACKAGE LABEL.PRINCIPAL DISPLAY PANEL

NDC 70771-1576-1

Triazolam Tablets USP, 0.125 mg

100 Tablets

Rx only

NDC 70771-1162- 1

Triazolam Tablets USP, 0.25 mg

100 Tablets

Rx only